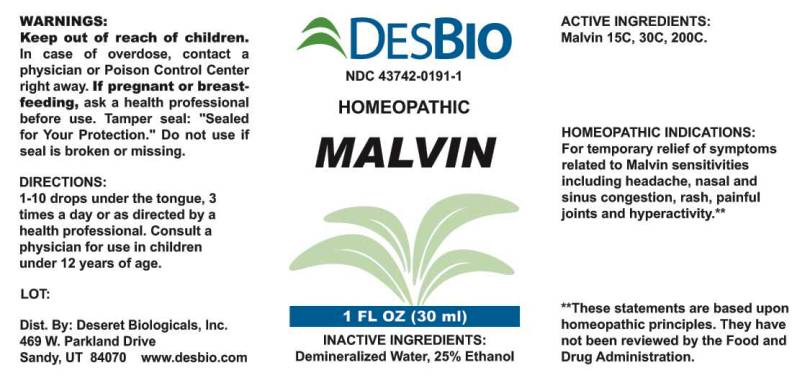 DRUG LABEL: Malvin
NDC: 43742-0191 | Form: LIQUID
Manufacturer: Deseret Biologicals, Inc.
Category: homeopathic | Type: HUMAN OTC DRUG LABEL
Date: 20240115

ACTIVE INGREDIENTS: MALVIN 15 [hp_C]/1 mL
INACTIVE INGREDIENTS: WATER; ALCOHOL

DRUG FACTS:

ACTIVE INGREDIENTS:

Malvin 15C, 30C, 200C.

HOMEOPATHIC INDICATIONS:

For temporary relief of symptoms related to Malvin sensitivities including headache, nasal and sinus congestion, rash, painful joints and hyperactivity.**

**These statements are based upon traditional homeopathic principles. They have not been reviewed by the Food and Drug Administration.

WARNINGS:

Keep out of reach of children. In case of overdose, contact physician or Poison Control Center right away.

If pregnant or breast-feeding, ask a health professional before use.

Tamper seal: "Sealed for Your Protection." Do not use if seal is broken or missing.

DIRECTIONS:

1-10 drops under the tongue, 3 times a day or as directed by a health professional. Consult a physician for use in children under 12 years of age.

INACTIVE INGREDIENTS:

Demineralized Water, 25% Ethanol.

KEEP OUT OF REACH OF CHILDREN: In case of overdose, contact physician or Poison Control Center right away.

HOMEOPATHIC INDICATIONS:

For temporary relief of symptoms related to Malvin sensitivities including headache, nasal and sinus congestion, rash, painful joints and hyperactivity.

QUESTIONS:

Dist. By: Deseret Biologicals, Inc.

469 Parkland Drive

Sandy, UT 84070 www.desbio.com

PACKAGE LABEL DISPLAY:

DESBIO

NDC 43742-0191-1

HOMEOPATHIC

MALVIN

1 FL OZ (30 ml)